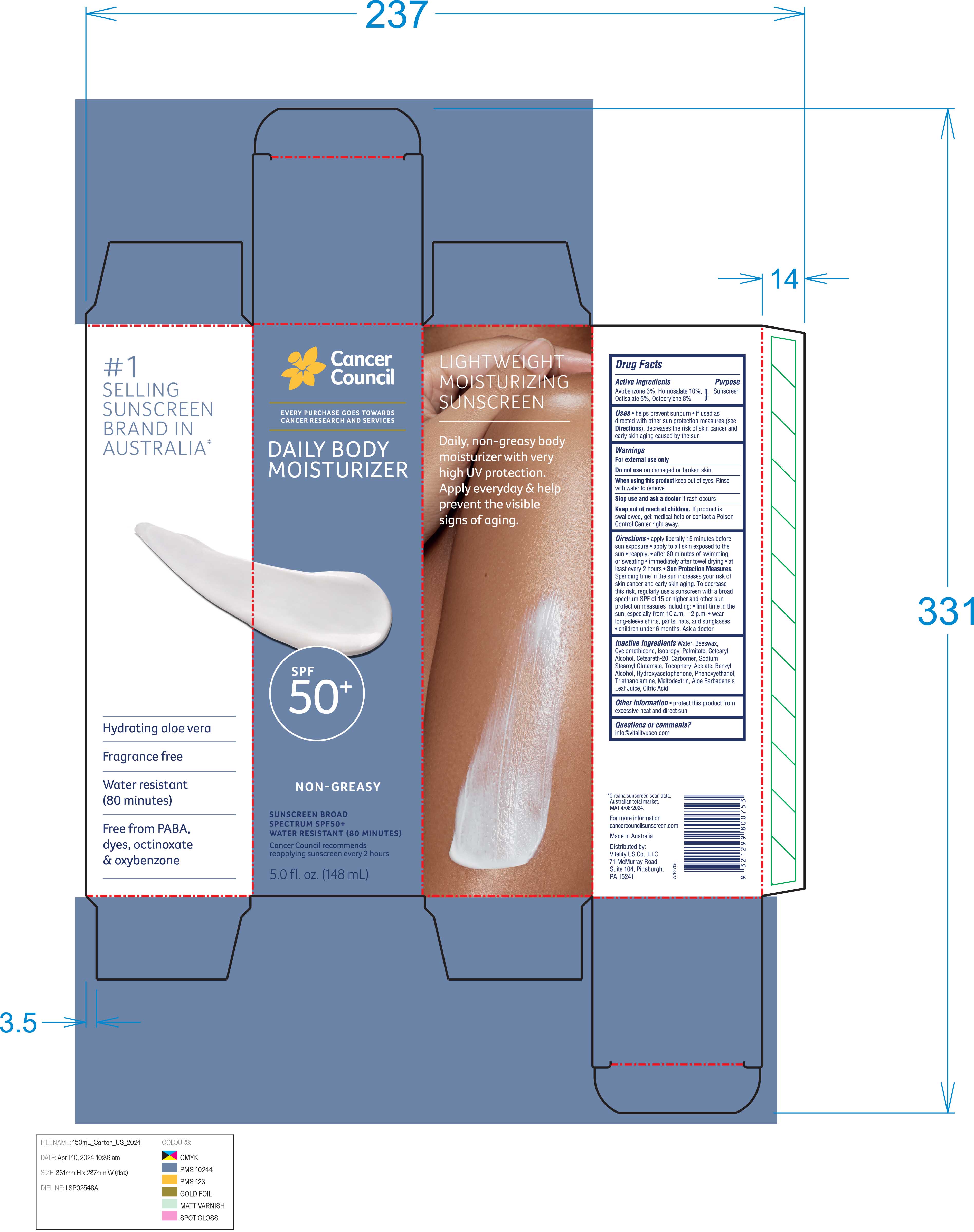 DRUG LABEL: Daily Body Moisturizer Sunscreen Broad Spectrum SPF 50
NDC: 70157-029 | Form: CREAM
Manufacturer: Baxter Laboratories Pty. Ltd.
Category: otc | Type: HUMAN OTC DRUG LABEL
Date: 20250905

ACTIVE INGREDIENTS: OCTOCRYLENE 8 g/100 mL; AVOBENZONE 3 g/100 mL; OCTISALATE 5 g/100 mL; HOMOSALATE 10 g/100 mL
INACTIVE INGREDIENTS: BEESWAX; CYCLOMETHICONE; BENZYL ALCOHOL; WATER; ISOPROPYL PALMITATE; CARBOMER; HYDROXYACETOPHENONE; .ALPHA.-TOCOPHEROL ACETATE; TRIETHANOLAMINE; ALOE BARBADENSIS LEAF JUICE; PHENOXYETHANOL; CETEARETH-20; CITRIC ACID; SODIUM STEAROYL GLUTAMATE; CETOSTEARYL ALCOHOL; MALTODEXTRIN

Daily Body Moisturizer Sunscreen Broad Spectrum SPF 50+

Active Ingredient Purpose

Avobenzone Sunscreen

Homosalate

Octisalate

Octocrylene

Uses

- Helps prevent sunburn
- If used as directed with other sun protection measures (see Directions), decreases the risk of skin cancer and early skin aging caused by the sun.

Keep out of reach of children. If Product is swallowed, get medical help or contact a Poison Control Center right away.

Stop use and ask a doctor if rash occurs

Warnings

For external Use Only

Do not use on damaged or broken skin

When using this product keep out of eyes. Rinse with water to remove.

Directions

- Apply liberally 15 minutes before sun exposure
- Apply to all skin exposed to the sun
- reapply:
- after 80 minutes of swimming or sweating
- Immediately after towel drying
- at least every 2 hours
- Sun Protection Measures. Spending time in the sun increases your risk of skin cancer and early skin aging. To decrease this risk, regularly use a sunscreen with a Broad Spectrum SPF value 15 or higher and other sun protection measures including:
- Limit time in the sun, especially from 10a.m. – 2p.m.
- Wear long-sleeve shirts, pants, hats, and sunglasses
- Children under 6 months: Ask a doctor

INACTIVE INGREDIENT

Inactive ingredients Water, Beeswax, Cyclomethicone, Isopropyl Palmitate, Cetearyl Alcohol, Ceteareth-20, Carbomer, Sodium Stearoyl Glutamate, Tocopheryl Acetate, Benzyl Alcohol, Hydroxyacetophenone, Phenoxyethanol, Triethanolamine, Maltodextrin, Aloe Barbadensis Leaf Juice, Citric Acid

Other information

- protect this product from excessive heat and direct sun

PACKAGE LABEL

Daily Body Moisturizer

SPF 50+

Non-Greasy

Sunscreen Broad Spectrum SPF50+

Water Resistant (80 Minutes)

5.0 fl. oz. (148 mL)